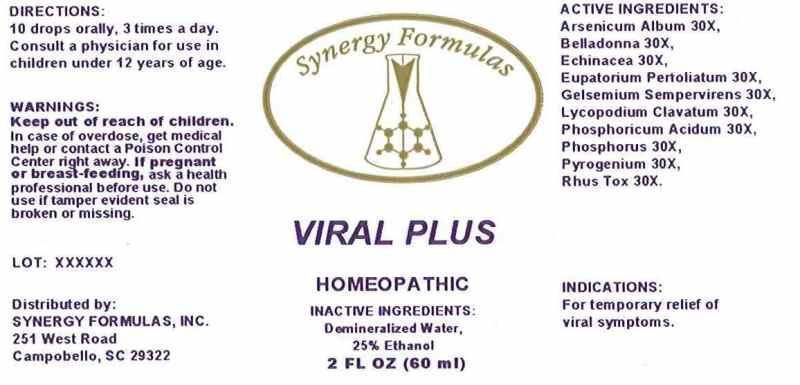 DRUG LABEL: Viral Plus
NDC: 43772-0040 | Form: LIQUID
Manufacturer: Synergy Formulas, Inc.
Category: homeopathic | Type: HUMAN OTC DRUG LABEL
Date: 20140715

ACTIVE INGREDIENTS: ARSENIC TRIOXIDE 30 [hp_X]/1 mL; ATROPA BELLADONNA 30 [hp_X]/1 mL; ECHINACEA ANGUSTIFOLIA 30 [hp_X]/1 mL; EUPATORIUM PERFOLIATUM FLOWERING TOP 30 [hp_X]/1 mL; GELSEMIUM SEMPERVIRENS ROOT 30 [hp_X]/1 mL; LYCOPODIUM CLAVATUM SPORE 30 [hp_X]/1 mL; PHOSPHORIC ACID 30 [hp_X]/1 mL; PHOSPHORUS 30 [hp_X]/1 mL; RANCID BEEF 30 1/1 mL; TOXICODENDRON PUBESCENS LEAF 30 [hp_X]/1 mL
INACTIVE INGREDIENTS: WATER; ALCOHOL

Drug Facts

ACTIVE INGREDIENTS:

Arsenicum album 30X, Belladonna 30X, Echinacea (Angustifolia) 30X, Eupatorium perfoliatum 30X, Gelsemium sempervirens 30X, Lycopodium clavatum 30X, Phosphoricum acidum 30X, Phosphorus 30X, Pyrogenium 30X, Rhus tox 30X.

INDICATIONS:

For the temporary relief of viral symptoms.

WARNINGS:

Keep out of reach of children. In case of overdose, get medical help or contact a Poison Control Center right away.

If pregnant or breast-feeding, ask a health professional before use.

Do not use if tamper evident seal is broken or missing.

Keep out of reach of children. In case of overdose, get medical help or contact a Poison Control Center right away.

DIRECTIONS:

10 drops orally, 3 times a day. Consult a physician for use in children under 12 years of age.

INDICATIONS:

For the temporary relief of viral symptoms.

INACTIVE INGREDIENTS:

Demineralized Water, 25% Ethanol.

QUESTIONS:

Distributed by:

SYNERGY FORMULAS, INC.

251 West Road

Campobello, SC 29322

PACKAGE LABEL DISPLAY:

Synergy Formulas

VIRAL PLUS

HOMEOPATHIC

2 FL OZ (60 ml)